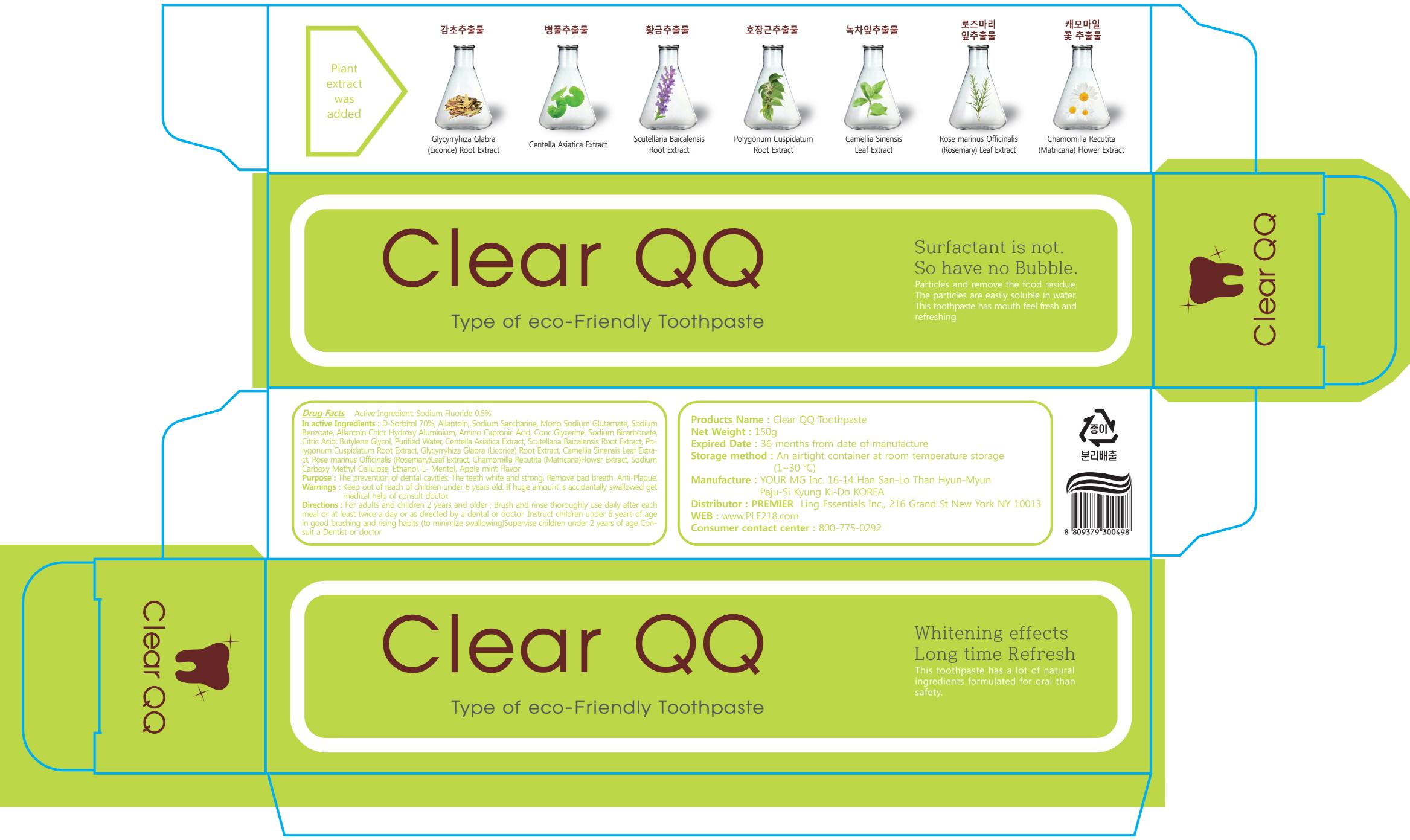 DRUG LABEL: Clear QQ
NDC: 70164-010 | Form: PASTE, DENTIFRICE
Manufacturer: YOURMG. CO. LTD
Category: otc | Type: HUMAN OTC DRUG LABEL
Date: 20151023

ACTIVE INGREDIENTS: Sodium Fluoride 0.75 g/150 g
INACTIVE INGREDIENTS: Allantoin; Sodium Bicarbonate

ACTIVE INGREDIENT

Active Ingredient: Sodium Fluoride 0.5%

INACTIVE INGREDIENT

Inactive Ingredients: D-Sorbitol 70%, Allantoin, Sodium Saccharine, Mono Sodium Glutamate, Sodium Benzoate, Allantoin Chlor Hydroxy Aluminium, Amino Capronic Acid, Conc Glycerine, Sodium Bicarbonate, Citric Acid, Butylene Glycol, Purified Water, Centella Asiatica Extract, Scutellaria Baicalensis Root Extract, Polygonum Cuspidatum Root Extract, Glycyrryhiza Glabra (Licorice) Root Extract, Camellia Sinensis Leaf Extract, Rose marinus Officinalis (Rosemary)Leaf Extract, Chamomilla Recutita (Matricaria)Flower Extract, Sodium Carboxy Methyl Cellulose, Ethanol, L- Mentol, Apple mint Flavor

PURPOSE

Purpose: The prevention of dental cavities. The teeth white and strong. Remove bad breath. Anti-plaque.

WARNINGS

Warnings: Keep out of reach of children under 6 years of age. If huge amount is accidentally swallowed get medical help of consult doctor.

Keep out of reach of children: Keep out of reach of children under 6 years of age.

INDICATIONS & USAGE

Directions: 1) Adults and children 2 years of age and older: Brush teeth throughly preferably after each meal or at least twice a day or as directed by a dentist or doctor. 2) Children under 6 years: To minimize swallowing, use a pea-sized amount and supervise brushing until good habits are established. 3) Children under 2 years: Consult a dentist or doctor

DOSAGE & ADMINISTRATION

Directions: 1) Adults and children 2 years of age and older: Brush teeth throughly preferably after each meal or at least twice a day or as directed by a dentist or doctor. 2) Children under 6 years: To minimize swallowing, use a pea-sized amount and supervise brushing until good habits are established. 3) Children under 2 years: Consult a dentist or doctor